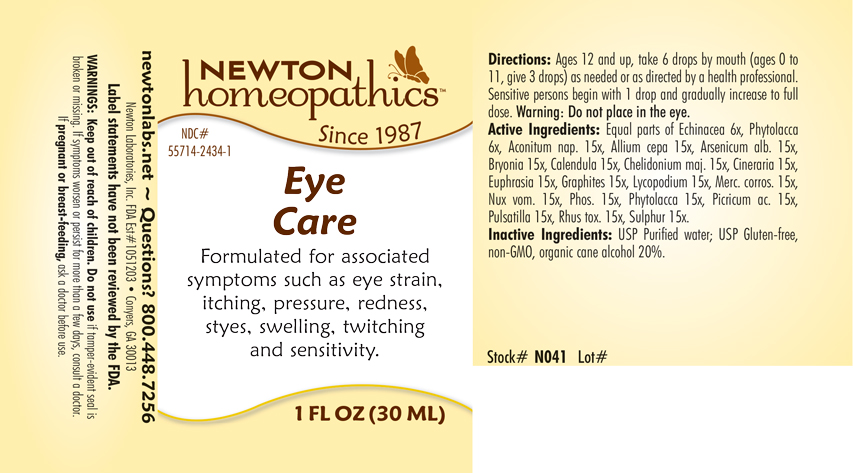 DRUG LABEL: Eye Care
NDC: 55714-2434 | Form: LIQUID
Manufacturer: Newton Laboratories, Inc.
Category: homeopathic | Type: HUMAN OTC DRUG LABEL
Date: 20201125

ACTIVE INGREDIENTS: ACONITUM NAPELLUS 15 [hp_X]/1 mL; ONION 15 [hp_X]/1 mL; ARSENIC TRIOXIDE 15 [hp_X]/1 mL; BRYONIA ALBA ROOT 15 [hp_X]/1 mL; CALENDULA OFFICINALIS FLOWERING TOP 15 [hp_X]/1 mL; CHELIDONIUM MAJUS 15 [hp_X]/1 mL; JACOBAEA MARITIMA 15 [hp_X]/1 mL; EUPHRASIA STRICTA 15 [hp_X]/1 mL; GRAPHITE 15 [hp_X]/1 mL; LYCOPODIUM CLAVATUM SPORE 15 [hp_X]/1 mL; MERCURIC CHLORIDE 15 [hp_X]/1 mL; STRYCHNOS NUX-VOMICA SEED 15 [hp_X]/1 mL; PHOSPHORUS 15 [hp_X]/1 mL; PHYTOLACCA AMERICANA ROOT 15 [hp_X]/1 mL; PULSATILLA VULGARIS 15 [hp_X]/1 mL; TOXICODENDRON PUBESCENS LEAF 15 [hp_X]/1 mL; SULFUR 15 [hp_X]/1 mL; ECHINACEA, UNSPECIFIED 6 [hp_X]/1 mL; PICRIC ACID 15 [hp_X]/1 mL
INACTIVE INGREDIENTS: ALCOHOL; WATER

Eye 2434L

INDICATIONS & USAGE SECTION

Formulated for associated symptoms such as eye strain, itching, pressure, redness, styes, swelling, twitching and sensitivity.

DOSAGE & ADMINISTRATION SECTION

Directions: Ages 12 and up, take 6 drops mouth (ages 0 to 11, give 3 drops) as needed or as directed by a health professional. Sensitive persons begin with 1 drop and gradually increase to full dose. Warning: Do not place in the eye.

OTC - ACTIVE INGREDIENT SECTION

Equal parts of Echinacea 6x, Phytolacca 6x, Aconitum nap. 15x, Allium cepa 15x, Arsenicum alb. 15x, Bryonia 15x, Calendula 15x, Chelidonium maj. 15x, Cineraria 15x, Euphrasia 15x, Graphites 15x, Lycopodium 15x, Merc. corros. 15x, Nux vom. 15x, Phos. 15x, Phytolacca 15x, Picricum ac. 15x, Pulsatilla 15x, Rhus tox. 15x, Sulphur 15x.

OTC - PURPOSE SECTION

Formulated for associated symptoms such as eye strain, itching, pressure, redness, styes, swelling, twitching and sensitivity.

INACTIVE INGREDIENT SECTION

Inactive Ingredients: USP Purified Water; USP Gluten-free, non-GMO, organic cane alcohol 20%.

QUESTIONS SECTION

newtonlabs.net – Questions? 800.448.7256

Newton Laboratories, Inc. FDA Est # 1051203 - Conyers, GA 30013

WARNINGS SECTION

WARNINGS: Keep out of reach of children. Do not use if tamper-evident seal is broken or missing. If symptoms worsen or persist for more than a few days, consult a doctor. If pregnant or breast-feeding, ask a doctor before use.

OTC - PREGNANCY OR BREAST FEEDING SECTION

If pregnant or breast-feeding, ask a doctor before use.

OTC - KEEP OUT OF REACH OF CHILDREN SECTION

Keep out of reach of children.